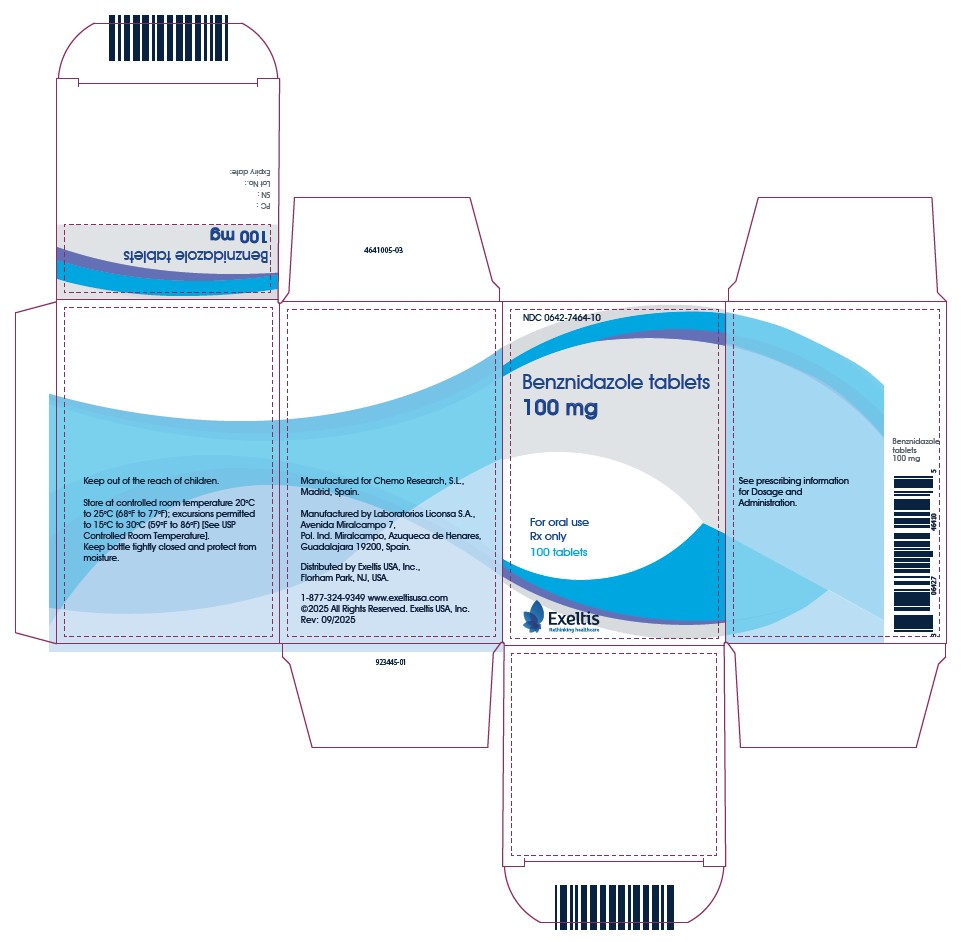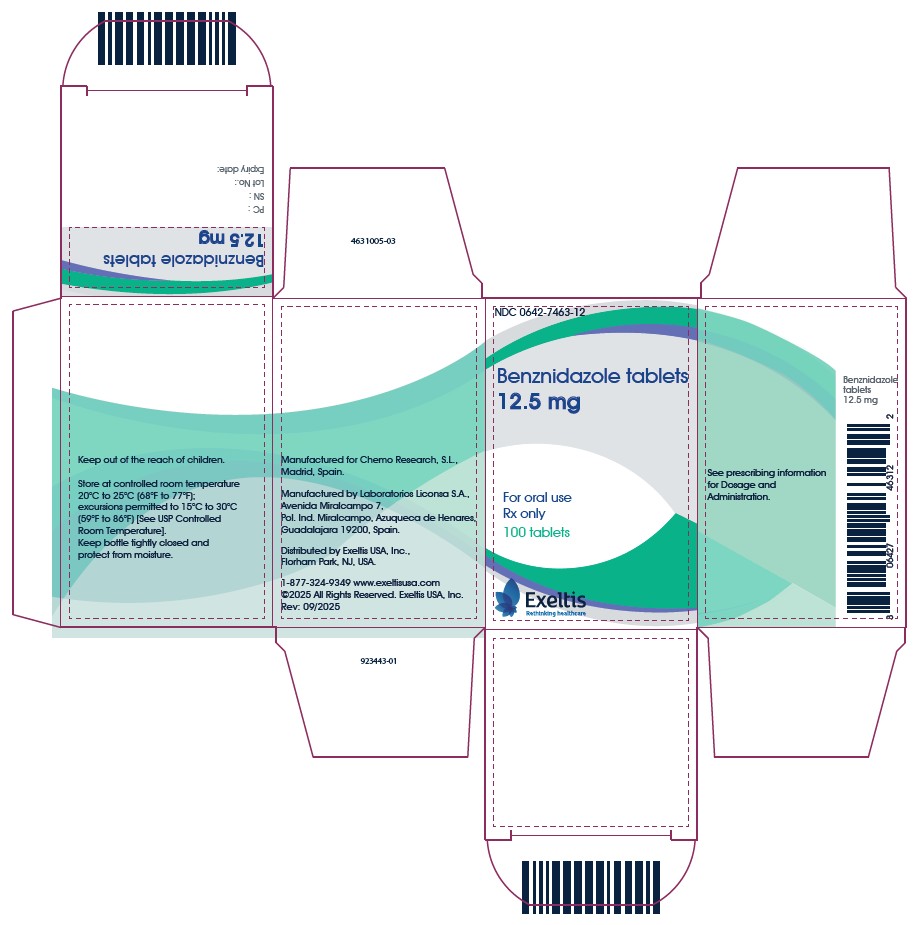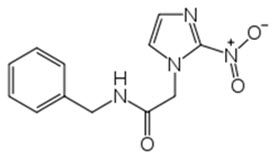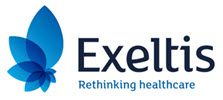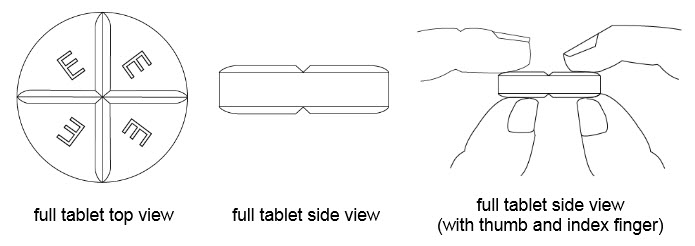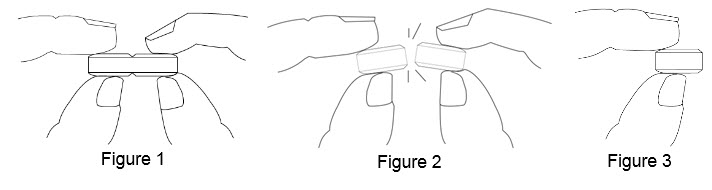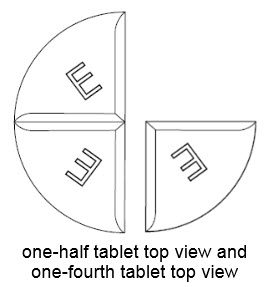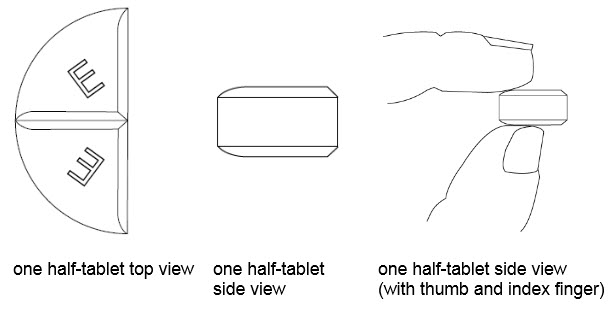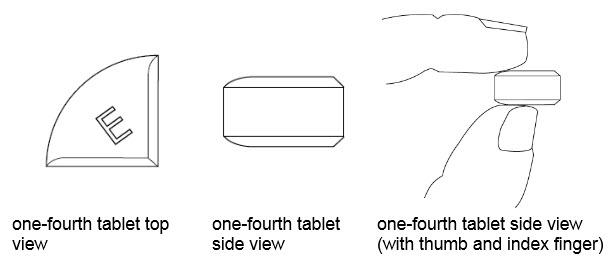 DRUG LABEL: Benznidazole
NDC: 0642-7463 | Form: TABLET
Manufacturer: Exeltis USA, Inc.
Category: prescription | Type: HUMAN PRESCRIPTION DRUG LABEL
Date: 20250915

ACTIVE INGREDIENTS: BENZNIDAZOLE 12.5 mg/1 1
INACTIVE INGREDIENTS: MAGNESIUM STEARATE; MICROCRYSTALLINE CELLULOSE; LACTOSE MONOHYDRATE; STARCH, CORN; CROSCARMELLOSE SODIUM

HIGHLIGHTS OF PRESCRIBING INFORMATION

These highlights do not include all the information needed to use BENZNIDAZOLE TABLETS safely and effectively. See full prescribing information for BENZNIDAZOLE TABLETS.
BENZNIDAZOLE tablets, for oral use
Initial U.S. Approval: 2017

RECENT MAJOR CHANGES

Contraindications, Patients with Cockayne Syndrome (4.3, 6.2) 12/2021

1 INDICATIONS AND USAGE

Benznidazole Tablets, a nitroimidazole antimicrobial, is indicated in pediatric patients 2 to 12 years of age for the treatment of Chagas disease (American trypanosomiasis), caused by Trypanosoma cruzi (1).

This indication is approved under accelerated approval based on the number of treated patients who became Immunoglobulin G (IgG) antibody negative against the recombinant antigens of T. cruzi. Continued approval for this indication may be contingent upon verification and description of clinical benefit in confirmatory trials (1, 14).

2 DOSAGE AND ADMINISTRATION

- Pediatric patients 2 to 12 years of age: The total daily dose is 5 mg/kg to 8 mg/kg orally administered in two divided doses separated by approximately 12 hours for a duration of 60 days (2.2).
- See Full Prescribing Information for important administration instructions (2.1, 2.3, 2.4).

3 DOSAGE FORMS AND STRENGTHS

- Tablets: 100 mg (functionally scored) (3).
- Tablets: 12.5 mg (3).

4 CONTRAINDICATIONS

• History of hypersensitivity reaction to benznidazole or other nitroimidazole derivatives (4.1).

• Disulfiram usage within the last two weeks (4.2).

• Patients with Cockayne Syndrome (4.3, 6.2).

5 WARNINGS AND PRECAUTIONS

- Potential Risk for Genotoxicity and Carcinogenicity (5.1).
- Embryo-Fetal Toxicity: Can cause fetal harm. Pregnancy testing is recommended for females of reproductive potential. Advise females of reproductive potential of the potential risk to a fetus and to use effective contraception (2.3, 5.2, 8.1, 8.3).
- Hypersensitivity skin reactions have been reported with benznidazole. In case of skin reactions, presenting with additional symptoms of systemic involvement such as lymphadenopathy, fever and/or purpura, discontinuation of treatment is recommended (5.3).
- Treatment with Benznidazole Tablets can potentially cause paresthesia or symptoms of peripheral neuropathy. In cases where neurological symptoms occur, immediate discontinuation of treatment is recommended (5.4).
- There have been hematological manifestations of bone marrow depression, such as neutropenia, thrombocytopenia, anemia, and leukopenia (5.5).

6 ADVERSE REACTIONS

Most common adverse reactions observed were abdominal pain, rash, decreased weight, headache, nausea, vomiting, neutropenia, urticaria, pruritus, eosinophilia, decreased appetite (6.1).

To report SUSPECTED ADVERSE REACTIONS, contact Exeltis USA, Inc. at 1-877-324-9349 or FDA at 1-800-FDA-1088 or www.fda.gov/medwatch.

8 USE IN SPECIFIC POPULATIONS

Lactation: Breastfeeding is not recommended (8.2).

FULL PRESCRIBING INFORMATION

1 INDICATIONS AND USAGE

Benznidazole Tablets are indicated in pediatric patients 2 to 12 years of age for the treatment of Chagas disease (American trypanosomiasis) caused by Trypanosoma cruzi.

This indication is approved under accelerated approval based on the number of treated patients who became Immunoglobulin G (IgG) antibody negative against the recombinant antigens of T. cruzi [see Clinical Studies (14)] . Continued approval for this indication may be contingent upon verification and description of clinical benefit in confirmatory trials.

2 DOSAGE AND ADMINISTRATION

2.1 Important Administration Instructions

- Benznidazole Tablets (12.5 mg and 100 mg) are for oral use and may be taken with or without food [see Clinical Pharmacology (12.3)] .
- Benznidazole Tablets are dosed by body weight (kg) [see Dosage and Administration (2.2)] .
- Benznidazole Tablets 100 mg are functionally scored tablets which can be split into one-half (50 mg) or one-quarter (25 mg) at the scored lines to provide doses less than 100 mg [see Instructions for Use] .
- Benznidazole Tablets 12.5 mg and 100 mg can be made into slurry as an alternative method of administration [see Dosage and Administration (2.4)] .

2.2 Recommended Dosage in Pediatric Patients (2 to 12 Years of Age)

The total daily dose for pediatric patients 2 to 12 years of age is 5 mg/kg to 8 mg/kg orally administered in two divided doses separated by approximately 12 hours, for a duration of 60 days (see Table 1).

Table 1: Recommended Dosage of Benznidazole Tablets in Pediatric Patients (2 to 12 Years of Age)
Body Weight Range (kg) | Dose (mg) | Number of Benznidazole Tablets 12.5 mg | Number of Benznidazole Tablets 100mg | Duration and Frequency of Therapy
Less than 15 kg | 50 mg | 4 tablets | ½ tablet | Administered twice daily approximately 12 hours apart for 60 days.
15 kg to less than 20 kg | 62.5 mg | 5 tablets |  | Administered twice daily approximately 12 hours apart for 60 days.
20 kg to less than 30 kg | 75 mg | 6 tablets | ¾ tablet | Administered twice daily approximately 12 hours apart for 60 days.
30 kg to less than 40 kg | 100 mg |  | 1 tablet | Administered twice daily approximately 12 hours apart for 60 days.
40 kg to less than 60 kg | 150 mg |  | 1 ½ tablets | Administered twice daily approximately 12 hours apart for 60 days.
Greater than or equal to 60 kg | 200 mg |  | 2 tablets

2.3 Assessment Prior to Initiating Benznidazole Tablets

Obtain a pregnancy test in females of reproductive potential prior to therapy with Benznidazole Tablets [see Use is Specific Populations (8.3)] .

2.4 Preparation of Slurry as an Alternative Method of Administration

A. Preparation of Slurry Using Benznidazole Tablets 12.5 mg for the Pediatric Population with Body Weight Less Than 30 kg

Benznidazole Tablets 12.5 mg may be made into slurry in a specified volume of water for the pediatric population with body weight less than 30 kg (see Table 2). The 12.5 mg tablet slurry is prepared by the following method:

Table 2: Preparation and Administration of Slurry Using Benznidazole Tablets 12.5 mg for the Pediatric Population with Body Weight of Less than 30 kg
- Place the prescribed dose of Benznidazole Tablets 12.5 mg into a cup.
- Add the specified volume of water per number of 12.5 mg tablets as shown below.
Body Weight Range (kg) | Dose (mg) | Number of Benznidazole Tablets 12.5 mg | Quantity of Water for Preparing the Slurry
Less than 15 kg | 50 mg | 4 tablets | 40 mL
15 kg to less than 20 kg | 62.5 mg | 5 tablets | 50 mL
20 kg to less than 30 kg | 75 mg | 6 tablets | 60 mL
- Allow the tablets to disintegrate in the cup over a period of approximately 1-2 minutes.
- Shake the contents of the cup gently to mix.
- Drink the contents of the cup (slurry of tablets with water) immediately.
- Rinse the cup with an additional 10 mL of water and drink the whole amount.

B. Preparation of Slurry Using Benznidazole Tablets 100 mg for the Pediatric Population with Body Weight (30 kg or greater)

Benznidazole Tablets 100 mg may be made into a slurry in a specified volume of water for the pediatric population with body weight of 30 kg or greater (see Table 3). The 100 mg tablet slurry is prepared as follows:

Table 3: Preparation and Administration of Slurry Using Benznidazole Tablets 100 mg for the Pediatric Population with Body Weight 30 kg or greater
- Place the prescribed dose of Benznidazole Tablets 100 mg tablets into a cup.
- Add the specified volume of water per number of 100 mg tablets as shown below.
Body Weight Range (kg) | Dose (mg) | Number of Benznidazole Tablets 100 mg | Quantity of Water for Preparing the Slurry
30 kg to less than 40 kg | 100 mg | 1 tablet | 80 mL
40 kg to less than 60 kg | 150 mg | 1 ½ tablets | 120 mL
Greater than or equal to 60 kg | 200 mg | 2 tablets | 160 mL
- Allow the tablet(s) to disintegrate in the cup over a period of approximately 1- 2 minutes.
- Shake the contents of the cup gently to mix.
- Drink the contents of the cup (slurry of tablet(s) with water) immediately.
- Rinse the cup by adding 80 mL of water and drink the whole amount. Repeat this rinse with 80 mL of water and drink again.

3 DOSAGE FORMS AND STRENGTHS

Benznidazole Tablets are available as 100 mg and 12.5 mg tablets.

The 100 mg white tablets are round and functionally scored twice as a cross on both sides, debossed with “E” on one side of each quarter portion.

The 12.5 mg white tablets are round and unscored, debossed with “E” on one side.

4 CONTRAINDICATIONS

4.1 Hypersensitivity

Benznidazole Tablets are contraindicated in patients with a history of hypersensitivity reaction to benznidazole or other nitroimidazole derivatives. Reactions have included severe skin and soft tissue reactions [see Adverse Reactions (6.1)] .

4.2 Disulfiram

Benznidazole Tablets are contraindicated in patients who have taken disulfiram within the last two weeks. Psychotic reactions may occur in patients who are using benznidazole and disulfiram concurrently [see Drug Interactions (7.1)] .

4.3 Patients with Cockayne Syndrome

Benznidazole Tablets are contraindicated in patients with Cockayne syndrome. Severe irreversible hepatotoxicity/acute liver failure with fatal outcomes have been reported after initiation of metronidazole, another nitroimidazole drug, structurally related to benznidazole in patients with Cockayne syndrome [see Adverse Reactions (6.2)] .

5 WARNINGS AND PRECAUTIONS

5.1 Potential for Genotoxicity and Carcinogenicity

Genotoxicity

Genotoxicity of benznidazole has been demonstrated in humans, in vitro in several bacterial species and mammalian cell systems, and in vivo in rodents [see Nonclinical Toxicology (13.1)] .

A study evaluating the cytogenetic effect of benznidazole in pediatric patients ranging from 11 months to 11 years of age (the safety and effectiveness of Benznidazole Tablets in patients less than 2 years old has not been established) with Chagas disease demonstrated a two-fold increase in chromosomal aberrations. In pediatric patients with Chagas disease who were treated with benznidazole, the median incidence of micronucleated interphase lymphocytes in 20 patients increased 2-fold compared to pre-dose values. In the same study, the mean incidence of chromosomal aberrations in 10 patients also increased 2-fold compared to pre-dose values.

Carcinogenicity

Carcinogenicity has been observed in mice and rats treated chronically with nitroimidazole agents which are structurally similar to benznidazole. Similar data have not been reported for benznidazole [see Nonclinical Toxicology (13.1)] . It is not known whether benznidazole is associated with carcinogenicity in humans.

5.2 Embryo-Fetal Toxicity

Based on findings from animal studies, Benznidazole Tablets can cause fetal harm when administered to a pregnant woman. In animal reproduction studies, benznidazole administered orally to pregnant rats and rabbits during organogenesis was associated with fetal malformations at doses approximately 1-3 times the maximum recommended human dose (MRHD) in rats (anasarca, anophthalmia, and/or microphthalmia) and doses approximately 0.3-1 times the MRHD in rabbits (ventricular septal defect). In rats, reduced maternal weights and smaller litter sizes occurred at a dose approximately 3 times the MRHD. In rabbits, reduced maternal weight gain, and abortions in 2/20 females occurred at a dose approximately equal to the MHRD [see Use in Specific Populations (8.1)] . Advise pregnant women of the potential risk to a fetus. Pregnancy testing is recommended for females of reproductive potential [see Dosage and Administration (2.3)] . Advise females of reproductive potential to use effective contraception during treatment with Benznidazole Tablets and for 5 days after the last dose [see Use in Specific Populations (8.1, 8.3) and Clinical Pharmacology (12.3)] .

5.3 Hypersensitivity Skin Reactions

Serious skin and subcutaneous disorders including acute generalized exanthematous pustulosis (AGEP), toxic epidermal necrolysis (TEN), erythema multiforme, and drug reaction with eosinophilia and systemic symptoms (DRESS) have been reported with benznidazole. Discontinue treatment at the first evidence of these serious cutaneous reactions [see Adverse Reactions (6.2)] .

Extensive skin reactions, such as rash (maculopapular, pruritic macules, eczema, pustules, erythematous, generalized, and allergic dermatitis, exfoliative dermatitis) have also been reported. Most cases occurred after approximately 10 days of treatment with benznidazole. Most rashes resolved with treatment discontinuation.

In case of skin reactions presenting with additional symptoms or signs of systemic involvement such as lymphadenopathy, fever and/or purpura, discontinuation of treatment is recommended.

5.4 Central and Peripheral Nervous System Effects

Treatment with Benznidazole Tablets can cause paresthesia or symptoms of peripheral neuropathy that may take several months to resolve. Headache and dizziness have been reported. In cases where neurological symptoms occur, immediate discontinuation of treatment is recommended. In most cases, symptoms occur late in the course of treatment.

5.5 Hematological Manifestations of Bone Marrow Depression

There have been reports of hematological manifestations of bone marrow depression, such as neutropenia, thrombocytopenia, anemia and leukopenia, which resolved after treatment discontinuation [see Adverse Reactions (6.1)] . Patients with hematological manifestations of bone marrow depression must take Benznidazole Tablets only under strict medical supervision. Monitor complete blood count. Total and differential leukocyte counts are recommended before, during and after therapy.

6 ADVERSE REACTIONS

The following serious and otherwise important adverse reactions are discussed in greater detail in other sections of labeling:

- Potential for Genotoxicity, Carcinogenicity, and Mutagenicity [see Warnings and Precautions (5.1)]
- Hypersensitivity Skin Reactions [see Warnings and Precautions (5.3)]
- Central and Peripheral Nervous System Effects [see Warnings and Precautions (5.4)]
- Hematological Manifestations of Bone Marrow Depression [see Warnings and Precautions (5.5)]

6.1 Clinical Trial Experience

Because clinical trials are conducted under widely varying conditions, adverse reaction rates observed in the clinical trials of a drug cannot be directly compared to rates in the clinical trials of another drug and may not reflect the rates observed in practice.

Benznidazole was evaluated in two randomized, double-blind, placebo-controlled trials (Trial 1^1 and Trial 2^2) and one uncontrolled trial (Trial 3^3).

Trial 1 was conducted in pediatric patients 6 to 12 years of age with chronic indeterminate Chagas disease in Argentina. The chronic indeterminate form includes patients with serologic evidence of T. cruzi infection without symptoms of cardiac or gastrointestinal disease. A total of 106 patients were randomized to receive either benznidazole (5 mg/kg/day twice daily for 60 days; N= 55) or placebo (N=51) and followed for 4 years.

Trial 2 was conducted in pediatric patients 7 to 12 years of age with chronic indeterminate Chagas disease in Brazil. A total of 129 patients were randomized to receive either benznidazole (7.5 mg/kg/day twice daily for 60 days; N = 64) or placebo (N = 65) and followed for 3 years.

Trial 3 was an uncontrolled study in pediatric patients 2 to 12 years of age with chronic indeterminate Chagas disease. A total of 37 pediatric patients with Chagas disease were enrolled in this safety and pharmacokinetics study. Patients were treated with benznidazole 5 to 8 mg/kg/day twice daily for 60 days.

Adverse Reactions Leading to Discontinuation

In Trial 1, benznidazole was discontinued due to an adverse reaction in 5/55 (9%) patients. Some patients had more than one adverse reaction resulting in treatment discontinuation. The adverse reactions included abdominal pain, nausea, vomiting, rash, decreased appetite, headache, and transaminases increased.

Common Adverse Reactions in Pediatric Patients

The most frequently reported adverse reactions in pediatric patients treated with benznidazole in Trial 1 were abdominal pain (25%), rash (16%), decreased weight (13%), and headache (7%). Table 4 lists adverse reactions occurring at a rate of 1% or greater in pediatric patients with Chagas disease aged 6 to 12 years of age in Trial 1.

Table 4: Adverse Reactions Occurring in Pediatric Patients with Chagas Disease aged 6 to 12 Years in Trial 1
Body System | Adverse Reaction | Benznidazole; (N=55) N (%) | Placebo; (N=51) N (%)
Gastrointestinal | Abdominal pain | 14 (25) | 4 (8)
 | Weight decreased | 7 (13) | 1 (2)
 | Nausea | 3 (5) | 1 (2)
 | Vomiting | 3 (5) | 0
 | Diarrhea | 2 (4) | 0
 | Decreased appetite | 3 (5) | 0
Skin and subcutaneous tissue | Rash | 9 (16) | 0
Metabolism/Laboratory | Transaminases increased | 3 (5) | 0
Nervous system Disorders | Dizziness | 2 (4) | 2 (4)
 | Peripheral neuropathy | 1 (2) | 0
 | Tremor | 1 (2) | 0

In Trial 2, skin lesions were reported in 7 of 64 (11%) pediatric patients treated with benznidazole and in 2 of 65 patients receiving placebo. Adverse reactions reported in fewer than 5% of benznidazole-treated patients included nausea, anorexia, headache, abdominal pain and arthralgia.

In a subset of 19 pediatric patients 2 to 6 years of age treated with benznidazole in Trial 3, 6 patients (32%) had the following adverse reactions: rash, leukopenia, urticaria, eosinophilia, decreased appetite, and neutropenia. These adverse reactions were similar to those observed in the overall population of 37 patients.

6.2 Postmarketing Experience

The following adverse reactions have been identified during the use of other formulations of benznidazole outside of the United States, or other nitroimidazole agents . Because these reactions are reported from a population of uncertain size, it is not always possible to reliably estimate their frequency or establish a causal relationship to drug exposure.

Other Formulations of Benznidazole:

Table 5: Adverse Reactions Reported in the Published Literature
Body System | Adverse Reactions
Dermatological | - Maculo-papular cutaneous eruptions - Erythematous plaques - Rash, generalized - Rash, erythematous - Pruritic rash - Blistering eruptions - Peeling skin - Exfoliative dermatitis - Toxic epidermal necrolysis - AGEP - Erythema multiforme - Drug reaction with eosinophilia and systemic symptoms (DRESS)
Neurological (central and peripheral nervous system) | - Paresthesia - Hypoesthesia - Headaches - Insomnia - Convulsions - Inability to concentrate - Amnesia, temporary - Disorientation, temporary
Gastrointestinal | - Epigastric pain - Dry mouth - Ageusia
Hepatobiliary disorders | - Hepatitis - Toxic hepatitis
Skeletal Muscle | - Myalgia - Musculoskeletal pain - Migratory arthritis
General / Constitutional Symptoms | - Fever - Asthenia - Fatigue
Lymphatic | - Generalized edema - Eyelid edema - Edema in the extremities - Lymphadenopathy
Bone Marrow | - Thrombocytopenia - Granulocytopenia - Agranulocytosis
Metabolism / Laboratory | - Elevation of alkaline phosphatase - Elevation of bilirubin

Metronidazole, Another Nitroimidazole Agent, Structurally Related to Benznidazole

Cases of severe irreversible hepatotoxicity/acute liver failure, including cases with fatal outcomes with very rapid onset after initiation of systemic use of metronidazole, another nitroimidazole agent structurally related to benznidazole, have been reported in patients with Cockayne syndrome (latency from drug start to signs of liver failure as short as 2 days) [see Contraindications (4.3)] .

7 DRUG INTERACTIONS

7.1 Disulfiram

Psychotic reactions have been reported in patients who are concurrently taking disulfiram and nitroimidazole agents (structurally related to benznidazole, but not with benznidazole). Benznidazole Tablets should not be given to patients who have taken disulfiram within the last two weeks [see Contraindications (4.2)] .

7.2 Alcohol and Products Containing Propylene Glycol

In vitro studies showed that benznidazole, at concentrations from 0.03 μM to 100 μM, does not inhibit the enzymatic activity of human alcohol dehydrogenase (ALDH). Benznidazole Tablets are not expected to cause alcohol aversion or a disulfiram-like reaction as a result of ethanol ingestion.

8 USE IN SPECIFIC POPULATIONS

8.1 Pregnancy

Risk Summary

Based on findings from animal studies, Benznidazole Tablets may cause fetal harm when administered to a pregnant woman. Published postmarketing reports on benznidazole use during pregnancy are insufficient to inform a drug-associated risk of adverse pregnancy-related outcomes. There are risks to the fetus associated with Chagas Disease (see Clinical Considerations) . In embryo-fetal development studies, benznidazole administered orally to pregnant rats and rabbits during organogenesis was associated with fetal malformations at doses approximately 1-3 times the MRHD in rats (anasarca, anophthalmia, and/or microphthalmia) and doses approximately 0.3-1.0 times the MRHD in rabbits (ventricular septal defect). In pregnant rats administered benznidazole during gestation and through lactation, effects in first generation offspring included reduced fertility in individual males and reduced numbers of live embryos and fetuses in pregnant females at a maternal dose equivalent to approximately 1.5 times the MRHD (see Data) . Advise pregnant women of the potential risk to a fetus.

The estimated background risk of major birth defects and miscarriage for the indicated population is unknown. All pregnancies have a background risk of birth defect, loss, or other adverse outcomes. In the U.S. general population, the estimated background risk of major birth defects and miscarriage in clinically recognized pregnancies is 2 to 4% and 15 to 20%, respectively.

Clinical Considerations

Disease-associated Maternal and/or Embryo/Fetal Risk

Published data from case-control and observational studies on chronic Chagas disease during pregnancy are inconsistent in their findings. Some studies showed an increased risk of pregnancy loss, prematurity and neonatal mortality in pregnant women who have chronic Chagas disease while other studies did not demonstrate these findings. Chronic Chagas disease is usually not life-threatening. Since pregnancy findings are inconsistent, treatment of chronic Chagas disease during pregnancy is not recommended due to risk of embryo-fetal toxicity from Benznidazole Tablets.

Acute symptomatic Chagas disease is rare in pregnant women; however, symptoms may be serious or life-threatening. There have been reports of pregnant women with life-threatening symptoms associated with acute Chagas disease who were treated with benznidazole. If a pregnant woman presents with acute symptomatic Chagas disease, the risks versus benefits of treatment with Benznidazole Tablets to the mother and the fetus should be evaluated on a case-by-case basis.

Data

Animal Data

In an embryo-fetal toxicity study in pregnant rats, benznidazole was administered in oral doses of 15, 50, and 150 mg/kg/day during organogenesis (days 6-17 of gestation), and the high dose was associated with maternal weight loss, reduced fetal weights, and smaller litter sizes. Benznidazole was also associated with a low incidence of fetal malformations including anasarca in one fetus at a dose of 50 mg/kg/day and anasarca and eye abnormalities (anophthalmia and microphthalmia) in 5 fetuses in 5 litters at a high dose of 150 mg/kg/day (approximately equivalent to 1 and 3 times, respectively, the MRHD based on whole body surface area comparisons). No maternal toxicity was observed at a benznidazole dose of 50 mg/kg/day (approximately equal to the MRHD based on body surface area comparison), and no fetal toxicity was observed at a dose of 15 mg/kg/day (approximately equivalent to 0.3 times the MRHD based on whole body surface area comparison).

In an embryo-fetal study in pregnant rabbits benznidazole administered by oral (gavage) in doses of 2.5, 7.5, and 25 mg/kg/day during organogenesis (days 6 to 19 of gestation) was associated with maternal toxicity at the high dose, including reduced weight gain and food consumption and abortions in 2/20 females. Benznidazole was also associated with a low incidence of fetal abnormalities including ventricular septal defect in 2 fetuses in 2 litters at a dose of 7.5 mg/kg/day and in 1 fetus at a dose of 25 mg/kg/day (approximately equivalent to 0.3 and 1 times respectively the MRHD based on whole body surface area comparison).The benznidazole doses that were not associated with maternal and fetal toxicity in this study were 7.5 and 2.5 mg/kg/day respectively, which are respectively equivalent to approximately 0.3 and 0.1 times the MRHD based on whole body surface area comparison.

In a pre-postnatal study in rats, first generation (F1) pups born to dams administered 15, 50, and 75 mg/kg/day benznidazole from day 6 of gestation to day 20 of lactation demonstrated normal pre-weaning behavior, physical and functional development, neurological findings, and reproductive parameters. However, cesarean section data for the pregnant first generation (F1) females in the high-dose group included significantly higher pre-implantation loss and significantly lower mean values for corpora lutea counts, number of implantations, and number of live embryos. Also, small testes and/or epididymides were observed in 1/20 and 2/20 first generation males in the mid- and high-dose groups respectively, and two of the affected animals failed to mate or induce pregnancy. However, the mean values for mating performance, fertility index, testes weight, testes and epididymides sperm counts, and epididymal sperm motility and progression were not altered in any of the F1 males in benznidazole treatment groups. The number of live second generation (F2) fetuses born to F1 dams was reduced in the high-dose group. The benznidazole dose that was not associated with adverse effects was considered to be 50 mg/kg/day which is approximately equal to the MRHD based on whole body surface area comparison.

8.2 Lactation

Risk Summary

Limited published literature based on breast milk sampling reports that benznidazole is present in human milk at infant doses of 5.5 to 17% of the maternal weight-adjusted dosage and a milk/plasma ratio ranging between 0.3-2.79. There are no reports of adverse effects on the breastfed infant and no information on the effects of benznidazole on milk production. Because of the potential for serious adverse reactions, and transmission of Chagas disease, advise patients that breastfeeding is not recommended during treatment with Benznidazole Tablets.

8.3 Females and Males of Reproductive Potential

Pregnancy Testing

Pregnancy testing is recommended for females of reproductive potential.

Contraception

Females

Benznidazole Tablets can cause fetal harm when administered to a pregnant woman [see Use in Specific Populations (8.1)] . Advise females of reproductive potential to use effective contraception during treatment with Benznidazole Tablets and for 5 days after the final dose.

Infertility

Males

Based on findings in rats, Benznidazole Tablets may impair fertility in males of reproductive potential. In rats, the effects on fertility were reversible 22 weeks after dosing; however, the effects in humans are unknown [see Nonclinical Toxicology (13.1)] .

8.4 Pediatric Use

The safety and effectiveness of Benznidazole Tablets have been established in pediatric patients 2 to 12 years of age for the treatment of Chagas disease. Use in pediatric patients 2 to 12 years of age was established in two adequate and well-controlled trials in pediatric patients 6 to 12 years old with additional safety and pharmacokinetic data from pediatric patients 2 to 6 years of age [see Dosage and Administration (2.2), Adverse Reactions (6.1), Clinical Studies (14)] .

Safety and effectiveness in pediatric patients below the age of 2 years and above the age of 12 years have not been established.

8.6 Hepatic Impairment

Use of Benznidazole Tablets has not been evaluated in patients with hepatic impairment.

8.7 Renal Impairment

Use of Benznidazole Tablets has not been evaluated in patients with renal impairment.

11 DESCRIPTION

Benznidazole Tablets contain benznidazole, a nitroimidazole antimicrobial. The chemical name of benznidazole is N-benzyl-2-(2-nitro-1H-imidazol-1-yl) acetamide. The empirical formula is C12H12N4O3 and the molecular weight is 260.246 g/mol. The structural formula is:

Figure 1: Benznidazole Structure

Benznidazole is a yellowish, practically crystalline powder that is practically insoluble in water, sparingly soluble in acetone and ethanol, and slightly soluble in methanol.

Benznidazole Tablets are white round tablets each containing 12.5 mg or 100 mg of benznidazole, for oral use. The 100 mg white tablets are round and functionally scored twice as a cross on both sides debossed with “E” on one side of each quarter portion. The 12.5 mg white tablets are round and unscored debossed with “E” on one side.

The inactive ingredients are as follows: magnesium stearate, NF; microcrystalline cellulose, NF; monohydrate lactose, NF; pre-gelatinized corn starch, NF; and sodium croscarmellose, NF.

12 CLINICAL PHARMACOLOGY

12.1 Mechanism of Action

Benznidazole is a nitroimidazole antimicrobial drug [see Microbiology (12.4)] .

12.2 Pharmacodynamics

The pharmacodynamics of benznidazole is unknown.

12.3 Pharmacokinetics

Absorption

The absorption of benznidazole from three different 100 mg benznidazole preparations was comparable when administered as a single dose under fasting conditions in adult healthy volunteers (Table 6).

Table 6: Summary of Benznidazole Pharmacokinetic (PK) Parameters Following a Single Oral Dose of 100 mg Benznidazole Administered Under Fasting Conditions in Adult Healthy Volunteers.
 | Preparations for 100 mg Benznidazole Oral Dose
 | One Benznidazole 100 mg Tablet Taken Whole | Slurry prepared with one Benznidazole 100 mg Tablet | Slurry prepared with eight Benznidazole 12.5 mg Tablets
Parameter | Mean (SD) | Mean (SD) | Mean (SD)
Cmax (mg/L) | 2.4 (0.5) | 2.4 (0.4) | 2.4 (0.4)
Tmax a(h) | 2 (1-4) | 2 (0.5-4) | 2 (1 - 4.5)
AUC (mg*h/L) | 43.5 (9.0) | 41.8 (9.6) | 44.1 (11.8)

a Tmax is presented as median (range)

Effect of Food

Benznidazole Cmax and AUC were not affected by the administration of Benznidazole 100 mg tablet with a high-fat, high-caloric meal (approximately 1034 total kcal, 67 kcal from fat, 42 kcal from carbohydrates, 59 kcal from protein) compared with fasted conditions in adult healthy volunteers. Serum concentrations of benznidazole reached peak levels at 3.2 hours (1-10 hours) after administration of Benznidazole Tablets 100 mg tablet after a high-fat, high-caloric meal, and at 2.0 hours (0.5-4 hours) in fasted conditions [see Dosage and Administration (2.1)] .

Distribution

Protein binding is reported to be approximately 44 to 60 %. The mean blood:plasma radioactivity ratios, ranging from 0.63 to 1.10, suggest that there is no preferential distribution of benznidazole into the red blood cells. The apparent volume of distribution of benznidazole is approximately 45 L.

Elimination
The elimination half-life of benznidazole is approximately 13 hours in healthy volunteers following single dose. The apparent total clearance of benznidazole is about 2.3 L/h.

Metabolism
In plasma, benznidazole parent drug is the most abundant component, accounting for approximately 80% of the total drug related exposure and no major circulating metabolites were identified. The primary benznidazole metabolism pathway is indicated to be nitro reduction followed by glucuronidation.

Excretion

Following oral administration of 100 mg radiolabeled benznidazole, about 68% and 21% of the radioactivity is recovered in urine (6% of total dose as unchanged parent drug) and feces (unchanged parent drug not detected), respectively.

Specific Populations

The effect of sex, race, renal impairment, or hepatic impairment on the pharmacokinetics of benznidazole is unknown.

Drug Interaction Studies

In vitro studies showed that benznidazole is a P-gp substrate and does not notably induce Cytochrome P450 enzymes 1A2, 2B6, and 3A4 at concentrations up to 100 mcM.

12.4 Microbiology

Mechanism of Action

Benznidazole inhibits the synthesis of DNA, RNA, and proteins within the T. cruzi parasite. Studies suggest that benznidazole is reduced by a Type I nitroreductase (NTR) enzyme of T. cruzi producing a series of short-lived intermediates that may promote damage to several macromolecules including DNA. In mammalian cells, however, benznidazole is metabolized by reduction of the nitro group to an amino group by a Type II NTR enzyme. The precise mechanism of action is not known.

Antimicrobial Activity

Benznidazole is active against all three stages, trypomastigotes, amastigotes, and epimastigotes, of T. cruzi. However, the sensitivity of T. cruzi strains to benznidazole, from different geographic regions, may vary.

Resistance

Studies in vitro and in mice infected with T. cruzi suggest a potential for development of resistance to benznidazole.

The mechanisms of drug resistance appear to be multifactorial. These mechanisms include decreased activity due to a mutation in the nitroreductase (TcNTR) gene. Other mechanisms include higher efflux activity due to over expression of TcPGP1 and TcPGP2 genes that encode p-glycoprotein as well as TcABCG1 genes that encode ATP-binding cassette transporters. Also, some studies reported overexpression of other genes TcFeSOD-A and TcCyP19 that encode superoxide dismutase and cyclophilin, respectively, which have diverse biological function and may help parasite survival. However, the clinical relevance of these findings is not known.

13 NONCLINICAL TOXICOLOGY

13.1 Carcinogenesis, Mutagenesis, Impairment of Fertility

Carcinogenicity

Long-term carcinogenicity studies for benznidazole have not been performed.

Nitroimidazoles, which have similar chemical structures to benznidazole have been reported to be carcinogenic in mice and rats.

Genetic Toxicity

Genotoxicity of benznidazole has been demonstrated in vitro in several bacterial species and mammalian cell systems and in vivo in mammals.

Benznidazole was mutagenic in several strains of S. typhimurium (TA 100, 102 1535, 1537, 1538, 97, 98 99 53 and UTH8414), E.coli, and K. pneumoniae.

Benznidazole was genotoxic in several in vitro mammalian cell assays including a chromosome aberration assay in human lymphocytes and in sister chromatid exchange assays in human lymphocytes and in Human Hep G2 cells.

In vivo, benznidazole was shown to be positive for genotoxicity in a mouse bone marrow micronucleus assay, in mouse and human red blood cell micronucleus assays, in a mouse abnormal sperm head assay and in a human peripheral blood lymphocyte assay. However in other micronucleus studies in mice and rats, oral doses of benznidazole did not cause a significant increase in the frequency of chromosomal aberrations in bone marrow cells or micronuclei in peripheral blood cells.

Impairment of Fertility

In a 6-month, chronic repeated-dosing study with Wistar rats, benznidazole was shown to produce dose-dependent testicular and epididymal atrophy at a dose of 30 mg/kg/day (approximately equivalent to 0.6 times the MRHD based on whole body surface area comparisons). Aspermia was also evident in affected rats, but fertility was not assessed in this study. The benznidazole dose that was not associated with adverse effects in this study was considered to be 10 mg/kg/day (5 mg/kg twice daily) in males which is approximately 0.2-times the MRHD based on whole body surface area comparison. In other literature reports, benznidazole has been shown to cause testicular atrophy and inhibit spermatogenesis in pubertal and adult rats and mice^5-7.

In a male fertility study, benznidazole was administered by oral (gavage) administration in daily doses of 10, 30, and 100 mg/kg/day to male Wistar rats beginning 10 weeks before mating, through mating, and for two weeks after mating for a total of 14-weeks. At the end of the dosing period, testicular and epididymal weights and the percent of normal sperm were decreased in mid- and high-dose males compared to control values. Also altered gonadal function, mating behavior and reduced fertility associated with morphologically and functionally altered sperm and histological changes in the testes and epididymides was observed in high-dose males. However, after a 22-week treatment-free period, almost complete recovery was observed with fully restored fertility compared to control values. After the 22-week treatment-free period the remaining benznidazole-related effects included reduced testicular and epididymal weights (10-22% reduction in absolute weight) compared to control values at the high benznidazole dose of 100 mg/kg/day (equivalent to approximately 2 times the MRHD based on whole body surface area comparison). The benznidazole dose at which no adverse effect was observed was 10 mg/kg/day which is equivalent to approximately 0.2 times the MRHD based on whole body surface area comparison.

In a female fertility study, benznidazole was administered by oral gavage to female Wistar rats in doses of 15, 50, and 150 mg/kg/day for a 2-week pre-mating period, during mating, and through day 7 of gestation. The high dose was associated with transient lower body weight gain and food consumption. There were no benznidazole-related effects on mating performance or fertility and no adverse macroscopic or reproductive organ weight changes. However, higher post-implantation loss with lower live litter size was observed at the high dose of 150 mg/kg/day (equivalent to approximately 3 times the MRHD based on whole body surface area comparison). The benznidazole dose that was not associated with adverse effects for this study was considered to be 50 mg/kg/day which is approximately equivalent to the MRHD based on whole body surface area comparison.

13.2 Animal Toxicology and/or Pharmacology

Single oral dose toxicity studies in rats have established that benznidazole causes ultrastructural changes in the adrenal cortex, colon, esophagus, ovaries, and testis^(5, 8-11). In these tissues, these changes were associated with the presences of nitro reductase activity, the production of reactive metabolites, and/or covalent binding of metabolites.

Neurotoxicity including brain axonal degeneration and Purkinje cell degeneration was observed with repeated-oral dosing in dogs without adverse changes in peripheral nerves^12-14. Neurological signs included: apathy, hypertonia, hyperreflexia, ataxia, loss of balance, oscillatory movements of the trunk and head, strong contractions of the back and leg muscles, opisthotonos and nystagmus. Neurotoxicity was not observed in other test species, including mouse, rat, guinea pig, and rabbit.

14 CLINICAL STUDIES

The safety and effectiveness of benznidazole for the treatment of Chagas disease in patients 6 to 12 years of age was established in two adequate and well-controlled trials (Trial 1 and Trial 2) as described below.

Trial 1 was a randomized, double-blind, placebo-controlled trial in children 6 to 12 years of age with chronic indeterminate Chagas disease conducted in Argentina. The chronic indeterminate form of Chagas disease includes patients with serologic evidence of T. cruzi infection without symptoms of cardiac or gastrointestinal disease. A total of 106 patients were randomized to receive either benznidazole (5 mg/kg/day for 60 days) or placebo and followed for 4 years. Patients with at least two positive conventional serologic tests for antibodies to T. cruzi were included in the study. The conventional serologic tests used include indirect hemagglutination assay (IHA), immunofluorescence antibody assay (IFA), and/or enzyme linked immunosorbent assay (ELISA) and were based on the detection of antibodies against T. cruzi parasites.

Trial 2 was a randomized, double-blind, placebo-controlled trial in pediatric patients 7 to 12 years of age with chronic indeterminate Chagas disease conducted in Brazil. A total of 129 patients were randomized to receive either benznidazole (7.5 mg/kg/day for 60 days) or placebo and followed for 3 years. Patients with three positive conventional serologic tests for antibodies to T. cruzi were included in the study. The conventional serologic tests include IHA, IFA, and/or ELISA and were based on the detection of antibodies against T. cruzi parasites.

Both trials measured antibodies by conventional and nonconventional assays. The nonconventional assays include F29-ELISA and AT- chemiluminescence-ELISA that are based on detection of anti- T. cruzi IgG antibodies against the recombinant antigens, F29 and AT from the flagella of T. cruzi parasites. Benznidazole treatment resulted in a significantly higher percentage of seronegative patients by a nonconventional assay. Results at the end of follow-up are reported in the following table.

Table 7: Nonconventional ELISAa Serologic Status at End-of-Follow-Up (mITT populationb)
 | Benznidazole | Placebo | Difference (95% CI)c
Trial 1 | N=40 | N=37
Seronegative | 24 (60.0) | 5 (13.5) | 46.5 (24.5, 64.4)
Seropositive | 15 | 29
Missing | 1 | 3
Trial 2 | N=64 | N=65
Seronegative | 35 (54.7) | 3 (4.6) | 50.1 (35.8, 63.4)
Seropositive | 23 | 51
Missing | 6 | 11
a Enzyme-linked immunosorbent assay (F29 ELISA in Study Trial 1 and AT chemiluminescence-ELISA in Trial 2); the F29 and AT antigens represent antigens from the flagella of T. cruzi parasites.
b Modified intent to treat (mITT) population includes subjects who are positive for the assay at baseline;
c Exact confidence intervals presented.

In Trial 1 using conventional ELISA, 4 of 53 (7.5%) benznidazole subjects and 2 of 50 (4.0%) placebo subjects seroconverted to negative by the end of follow-up (difference 3.5, 95% CI (-7.0, 14.9)). In Trial 2 using conventional ELISA, 4 of 64 (6.3%) of benznidazole subjects and 0 of 65 placebo subjects seroconverted to negative by the end of follow-up (difference 6.3, 95% CI (0.3, 15.2)).

15 REFERENCES

1. Sosa Estani S, et al., 1998, Efficacy of Chemotherapy with Benznidazole in Children in the Indeterminate Phase of Chagas' Disease. Am J Trop Med Hyg 59: 526-529.
2. de Andrade, Ana Lucia S. Sgambatti, et al., 1996, Randomised Trial of Efficacy of Benznidazole in Treatment of Early Trypanosoma cruzi Infection. Lancet 348: 1407-1413.
3. Altcheh, Jaime, et al., 2014, Population Pharmacokinetic Study of Benznidazole in Pediatric Chagas Disease Suggests Efficacy Despite Lower Plasma Concentrations than in Adults. PLoS Negl Trop Dis 8:e2907.
4. García-Bournissen, F, S Moroni, ME Marson, et al., 2015, Limited Infant Exposure to Benznidazole Through Breast Milk During Maternal Treatment for Chagas Disease. Arch Dis Child 100:90-94.
5. Bernacchi, AS, CR de Castro, EG de Toranzo, and JA Castro, 1986, Effects of Nifurtimox or Benznidazole Administration on Rat Testes: Ultrastructural Observations and Biochemical Studies, Exp Mol Pathol 45: 245-256.
6. Vieira, CL, TL Lamano-Carvalho, AL Favaretto, MM Valenca, J Antunes-Rodridgues, and AA Barreira, 1989, Testes Alterations in Pubertal Benznidazole-treated Rats, Braz J Med Biol Res, 22: 695-698.
7. Navarro, ML and R Nagel, 1990, Abnormal Sperm Induced in Mice by Oral Administration of Antichagasic Drugs, Comunicaciones Biologicas, 8: 251-258.
8. de Castro, RC, EG Diaz de Toranzo, and JA Castro, 1992, Benznidazole-induced Ultrastructural Alterations in Rat Adrenal Cortex: Mechanistic Studies, Toxicology, 74: 223-232.
9. Diaz, EG, RC de Castro, M Montalto de Mecca, and JA Castro, 2000, Benznidazole-induced Ultrastructural and Biochemical Alterations in Rat Colon, Acta Pharmacol Sin, 21: 961-966.
10. de Castro, RC, M Montalto de Mecca, SL Fanelli, EC de Ferreyra, EG Diaz, and JA Castro, 2003, Benznidazole-induced Ultrastructural and Biochemical Alterations in Rat Esophagus, Toxicology, 191: 189-198.
11. de Castro, CR, EGD de Toranzo, AS Bernacchi, M Carbone, and JA Castro, 1989, Ultrastructural Alterations in Ovaries from Nifurtimox or Benznidazole-treated Rats: Their Relation to Ovarian Nitroreductive Biotransformation of Both Drugs, Exp Mol Pathol, 50: 385-397.
12. Scharer, K, 1972, Selective Purkinje Cell Damage in Dogs after Oral Administration of High Doses of Nitroimidazole Derivatives, Verhandlungen der Deutschen Gesellschaft fur Pathologie, 56: 407-10.
13. Flores-Vieira, CLL and AA Barreira, 1997a, Experimental Benznidazole Encephalopathy: I. Clinical-Neurological Alterations, J Neurol Sci, 150: 3-11.
14. Flores-Vieira, CLL, L Chimelli, RMF Fernandez, and AA Barreira, 1997b, Experimental Benznidazole Encephalopathy: II. Electroencephalographic and Morphological Alterations, J Neurol Sci, 150:13-25.

16 HOW SUPPLIED/STORAGE AND HANDLING

16.1 How Supplied

Benznidazole Tablets (12.5 mg or 100 mg) are supplied as follows:

- 100 mg white tablets, round and functionally scored twice as a cross on both sides. Each tablet is about 10 mm in diameter debossed with “E” on one side of each quarter portion.
- 12.5 mg white tablets, round and unscored. Each tablet is about 5 mm in diameter debossed with “E” on one side.

Benznidazole Tablets 100 mg are available in bottles of 100 tablets (NDC 0642-7464-10).

Benznidazole Tablets 12.5 mg are available in bottles of 100 tablets (NDC 0642-7463-12).

16.2 Storage and Handling

Store at controlled room temperature 20°C to 25°C (68°F to 77°F); excursions permitted to 15°C to 30°C (59°F to 86°F) [See USP Controlled Room Temperature]. Keep bottle tightly closed and protect from moisture.

17 PATIENT COUNSELING INFORMATION

Advise the patient to read the FDA-approved patient labeling (Instructions for Use).

Embryo-Fetal Toxicity

Advise pregnant women and females of reproductive potential that exposure to Benznidazole Tablets during pregnancy can result in fetal harm.

Advise females to inform their healthcare provider of a known or suspected pregnancy [see Warnings and Precautions (5.2) and Use in Specific Populations (8.1)] .

Advise females of reproductive potential to use effective contraception while taking

Benznidazole Tablets and for 5 days after the last dose [see Use in Specific Populations (8.3)] .

Lactation

Advise women not to breastfeed during treatment with Benznidazole Tablets [see Use in Specific Populations (8.2)] .

Infertility

Advise males of reproductive potential that Benznidazole Tablets may impair fertility [see Use in Specific Populations (8.3) and Nonclinical Toxicology (13.1)] .

Important Administration Instructions

Advise patients and parents/caregivers of pediatric patients taking Benznidazole Tablets that:

•Benznidazole Tablets 100 mg are functionally scored tablets which can be split into one-half (50 mg) or one-quarter (25 mg) at the scored lines to provide doses less than 100 mg.

•Benznidazole Tablets 12.5 mg and 100 mg (whole or split) can be made into a slurry in a specified volume of water for the pediatric population [see Dosage and Administration (2.3)] .

Hypersensitivity Skin Reactions

Advise patients that serious skin reactions can occur with Benznidazole Tablets. In case of skin reactions, presenting with additional symptoms of systemic involvement such as lymphadenopathy, fever and/or purpura, discontinuation of treatment is necessary.

Central and Peripheral Nervous System Effects

Advise patients that treatment can potentially cause paresthesia or symptoms of peripheral neuropathy. In cases where neurological symptoms occur, immediate discontinuation of treatment is recommended.

Hematological Manifestations of Bone Marrow Depression

Advise patients that there have been hematological manifestations of bone marrow depression, such as anemia and leukopenia, which are reversible, and normalized after treatment discontinuation.

Manufactured for Chemo Research, S.L.
Madrid, Spain

Manufactured by Laboratorios Liconsa S.A.
Guadalajara, Spain

Distributed by:

Exeltis USA, Inc.
Florham Park, NJ 07932

INSTRUCTIONS FOR USE

BENZNIDAZOLE
tablets, for oral use

Read this Instructions for Use before you start taking BENZNIDAZOLE and each time you get a refill. There may be new information. This information does not take the place of talking to your doctor about your medical condition or treatment.

Note:

• Your doctor may need to change your dose of BENZNIDAZOLE during treatment as needed.

• BENZNIDAZOLE 100 mg tablets can be taken whole or broken at scored lines.

• BENZNIDAZOLE 100 mg tablets are marked with scored lines and may be broken at these scored lines to provide the following doses: 75 mg, 50 mg and 25 mg.

100 mg treatment (take the whole tablet)

How to break your BENZNIDAZOLE 100 mg tablet:

• Hold the tablet between your thumbs and index fingers close to the scored line (See Figure 1).

• Apply enough pressure to break the tablet at the scored line (See Figure 2).

• Only use a tablet that has been broken at the scored line (See Figure 3).

• Do not break the BENZNIDAZOLE 100 mg tablet in any other way.

75 mg treatment (take one-half of the tablet and one-fourth of the tablet)

50 mg treatment (take one-half of the tablet)

25 mg treatment (take one-fourth of the tablet)

How should I store BENZNIDAZOLE?

• Store BENZNIDAZOLE at room temperature 20° to 25°C (68°to 77°F).

• Keep BENZNIDAZOLE in the bottle that it comes in and keep the bottle tightly closed.

• Keep BENZNIDAZOLE away from moisture.

Keep BENZNIDAZOLE and all medicines out of the reach of children.

This Instructions for Use has been approved by the U.S. Food and Drug Administration.

Manufactured by: Laboratori os Liconsa S.A., Guadalajara, Spain

Issued: August 2017

PRINCIPAL DISPLAY PANEL - 100 mg CARTON

NDC 0642-7464-10

Benznidazole tablets
100 mg

For oral use
Rx only
100 tablets

Exeltis
Rethinking healthcare

Keep out of the reach of children.

Store at controlled room temperature 20°C to 25°C (68°F to 77°F); excursions permitted to 15°C to 30°C (59°F to 86°F) [See USP Controlled Room Temperature].
Keep bottle tightly closed and protect from moisture.

Manufactured for Chemo Research, S.L.,
Madrid, Spain.

Manufactured by Laboratorios Liconsa S.A.,
Avenida Miralcampo 7,
Pol. Ind. Miralcampo, Azuqueca de Henares,
Guadalajara 19200, Spain.

Distributed by Exeltis USA, Inc.,
Florham Park, NJ, USA.

1-877-324-9349 www.exeltisusa.com
©2025 All Rights Reserved. Exeltis USA, Inc.

Rev: 09/2025

See prescribing information
for Dosage and
Administration.

Benznidazole
tablets
100 mg

Benznidazole tablets
100 mg

Lot No.:
Expiry date:

PRINCIPAL DISPLAY PANEL - 12.5 mg CARTON

NDC 0642-7463-12

Benznidazole tablets
12.5 mg

For oral use
Rx only
100 tablets

Exeltis
Rethinking healthcare

Keep out of the reach of children.

Store at controlled room temperature 20°C to 25°C (68°F to 77°F); excursions permitted to 15°C to 30°C (59°F to 86°F) [See USP Controlled Room Temperature].
Keep bottle tightly closed and protect from moisture.

Manufactured for Chemo Research, S.L.,
Madrid, Spain.

Manufactured by Laboratorios Liconsa S.A.,
Avenida Miralcampo 7,
Pol. Ind. Miralcampo, Azuqueca de Henares,
Guadalajara 19200, Spain.

Distributed by Exeltis USA, Inc.,
Florham Park, NJ, USA.

1-877-324-9349 www.exeltisusa.com
©2025 All Rights Reserved. Exeltis USA, Inc.

Rev: 09/2025

See prescribing information
for Dosage and
Administration.

Benznidazole
tablets
12.5 mg

Benznidazole tablets
12.5 mg

Lot No.:
Expiry date: